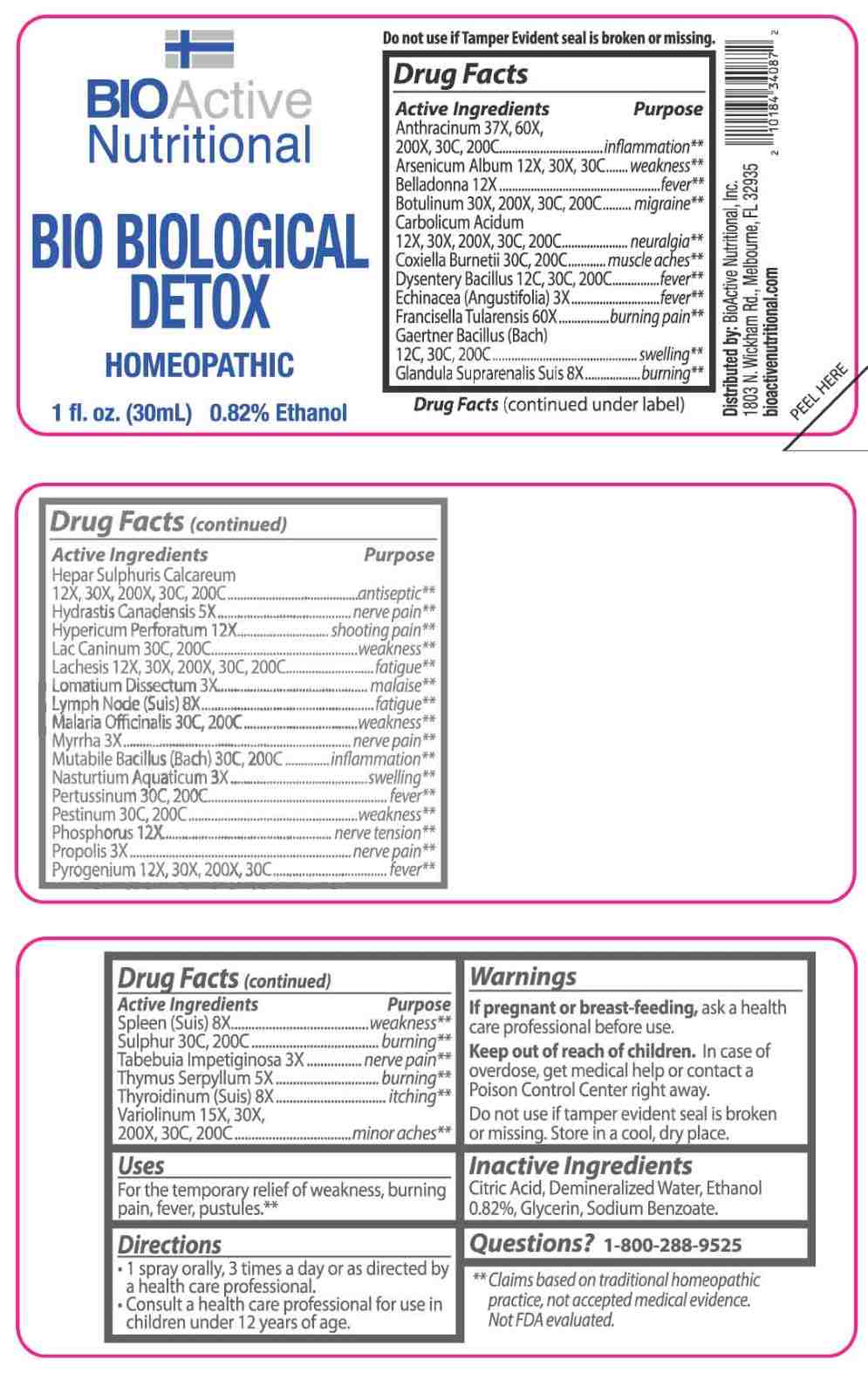 DRUG LABEL: Bio Biological Detox
NDC: 43857-0667 | Form: SPRAY
Manufacturer: BioActive Nutritional, Inc.
Category: homeopathic | Type: HUMAN OTC DRUG LABEL
Date: 20251230

ACTIVE INGREDIENTS: ECHINACEA ANGUSTIFOLIA WHOLE 3 [hp_X]/1 mL; LOMATIUM DISSECTUM ROOT 3 [hp_X]/1 mL; MYRRH 3 [hp_X]/1 mL; NASTURTIUM OFFICINALE 3 [hp_X]/1 mL; PROPOLIS WAX 3 [hp_X]/1 mL; HANDROANTHUS IMPETIGINOSUS BARK 3 [hp_X]/1 mL; GOLDENSEAL 5 [hp_X]/1 mL; THYMUS SERPYLLUM WHOLE 5 [hp_X]/1 mL; SUS SCROFA ADRENAL GLAND 8 [hp_X]/1 mL; SUS SCROFA LYMPH 8 [hp_X]/1 mL; SUS SCROFA SPLEEN 8 [hp_X]/1 mL; THYROID 8 [hp_X]/1 mL; ATROPA BELLADONNA 12 [hp_X]/1 mL; HYPERICUM PERFORATUM WHOLE 12 [hp_X]/1 mL; PHOSPHORUS 12 [hp_X]/1 mL; RANCID BEEF 12 [hp_X]/1 mL; BACILLUS ANTHRACIS IMMUNOSERUM RABBIT 37 [hp_X]/1 mL; ARSENIC TRIOXIDE 12 [hp_X]/1 mL; PHENOL 12 [hp_X]/1 mL; CALCIUM SULFIDE 12 [hp_X]/1 mL; LACHESIS MUTA VENOM 12 [hp_X]/1 mL; VARIOLA VIRUS 15 [hp_X]/1 mL; CLOSTRIDIUM BOTULINUM 30 [hp_X]/1 mL; SHIGELLA DYSENTERIAE 12 [hp_C]/1 mL; SALMONELLA ENTERICA ENTERICA SEROVAR ENTERITIDIS 12 [hp_C]/1 mL; FRANCISELLA TULARENSIS 60 [hp_X]/1 mL; COXIELLA BURNETII 30 [hp_C]/1 mL; CANIS LUPUS FAMILIARIS MILK 30 [hp_C]/1 mL; PLASMODIUM FALCIPARUM 30 [hp_C]/1 mL; ESCHERICHIA COLI 30 [hp_C]/1 mL; HUMAN SPUTUM, BORDETELLA PERTUSSIS INFECTED 30 [hp_C]/1 mL; YERSINIA PESTIS 30 [hp_C]/1 mL; SULFUR 30 [hp_C]/1 mL
INACTIVE INGREDIENTS: CITRIC ACID MONOHYDRATE; GLYCERIN; SODIUM BENZOATE; WATER; ALCOHOL

DRUG FACTS:

ACTIVE INGREDIENTS:

Anthracinum 37X, 60X, 200X, 30C, 200C, Arsenicum Album 12X, 30X, 30C, Belladonna 12X, Botulinum 30X, 200X, 30C, 200C, Carbolicum Acidum 12X, 30X, 200X, 30C, 200C, Coxiella Burnetii 30C, 200C, Dysentery Bacillus 12C, 30C, 200C, Echinacea (Angustifolia) 3X, Francisella Tularensis 60X, Gaertner Bacillus (Bach) 12C, 30C, 200C, Glandula Suprarenalis Suis 8X, Hepar Sulphuris Calcareum 12X, 30X, 200X, 30C, 200C, Hydrastis Canadensis 5X, Hypericum Perforatum 12X, Lac Caninum 30C, 200C, Lachesis 12X, 30X, 200X, 30C, 200C, Lomatium Dissectum 3X, Lymph Node (Suis) 8X, Malaria Officinalis 30C, 200C, Myrrha 3X, Mutabile Bacillus (Bach) 30C, 200C, Nasturtium Aquaticum 3X, Pertussinum 30C, 200C, Pestinum 30C, 200C, Phosphorus 12X, Propolis 3X, Pyrogenium 12X, 30X, 200X, 30C, Spleen (Suis) 8X, Sulphur 30C, 200C, Tabebuia Impetiginosa 3X, Thymus Serpyllum 5X, Thyroidinum (Suis) 8X, Variolinum 15X, 30X, 200X, 30C, 200C.

PURPOSE:

Anthracinum - inflammation,** Arsenicum Album - weakness,** Belladonna - fever,** Botulinum - migraine,** Carbolicum Acidum - neuralgia,** Coxiella Burnetii – muscle aches,** Dysentery Bacillus - fever,** Echinacea (Angustifolia) - fever,** Francisella Tularensis – burning pain,** Gaertner Bacillus (Bach) - swelling,** Glandula Suprarenalis Suis - burning,** Hepar Sulphuris Calcareum - antiseptic,** Hydrastis Canadensis – nerve pain,** Hypericum Perforatum – shooting pain,** Lac Caninum - weakness,** Lachesis - fatigue,** Lomatium Dissectum - malaise,** Lymph Node (Suis) - fatigue,** Malaria Officinalis - weakness,** Myrrha – nerve pain,** Mutabile Bacillus (Bach) - inflammation,** Nasturtium Aquaticum - swelling,** Pertussinum - fever,** Pestinum - weakness,** Phosphorus – nerve tension,** Propolis – nerve pain,** Pyrogenium - fever,** Spleen (Suis) - weakness,** Sulphur – burning,** Tabebuia Impetiginosa – nerve pain,** Thymus Serpyllum - burning,** Thyroidinum (Suis) - itching,** Variolinum – minor aches**

**Claims based on traditional homeopathic practice, not accepted medial evidence. Not FDA evaluated.

USES:

For temporary relief of weakness, burning pain, fever, pustules.**

**Claims based on traditional homeopathic practice, not accepted medial evidence. Not FDA evaluated.

WARNINGS:

If pregnant or breast-feeding, ask a health care professional before use.

Keep out of reach of children. In case of overdose, get medical help or contact a Poison Control Center right away.

Do not use if tamper evident seal is broken or missing.

Store in a cool, dry place.

KEEP OUT OF REACH OF CHILDREN:

In case of overdose, get medical help or contact a Poison Control Center right away.

DIRECTIONS:

• 1 spray orally, 3 times a day or as directed by a health care professional.

• Consult a health care professional for use in children under 12 years of age.

INACTIVE INGREDIENTS:

Citric Acid, Demineralized Water, Ethanol 0.82%, Glycerin, Sodium Benzoate.

QUESTIONS:

Distributed by:

BioActive Nutritional, Inc.

1803 N. Wickham Rd.

Melbourne, FL 32935

bioactivenutritional.com

1-800-288-9525

PACKAGE LABEL DISPLAY:

BIOActive Nutritional

BIO BIOLOGICAL DETOX

HOMEOPATHIC

1 fl. oz. (30 mL)